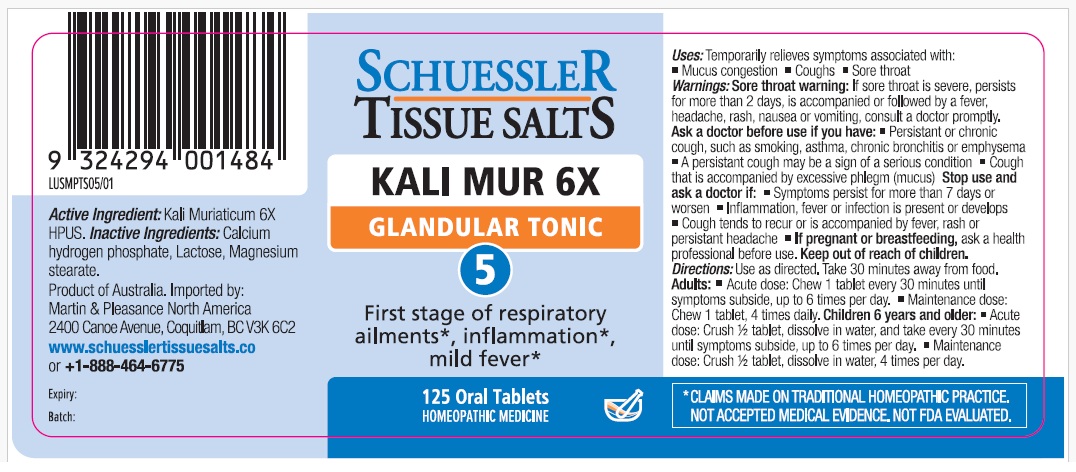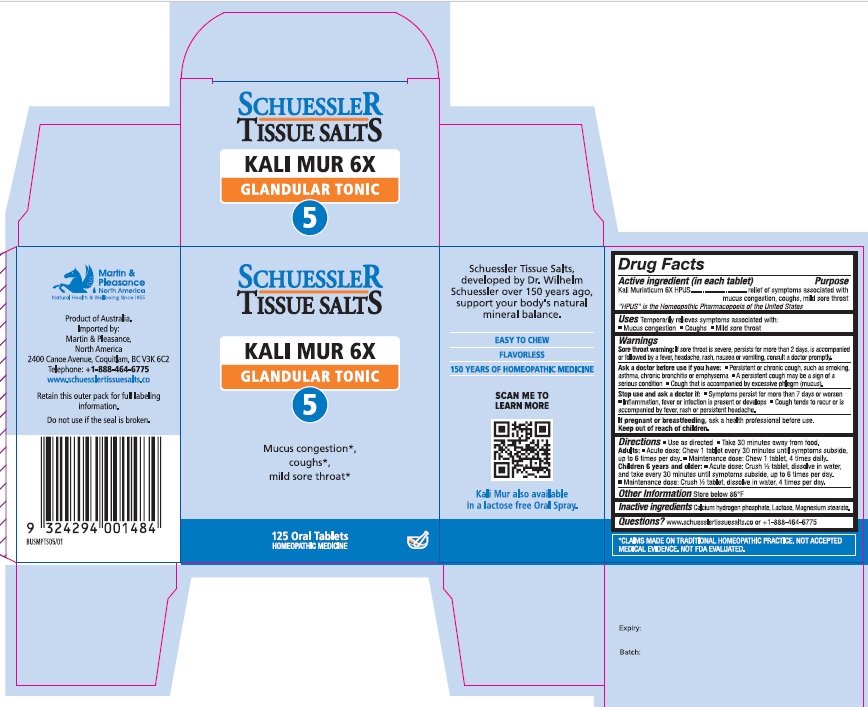 DRUG LABEL: Schuessler Tissue Salts Kali Mur Glandular Tonic 5
NDC: 84999-017 | Form: TABLET, CHEWABLE
Manufacturer: Martin & Pleasance Pty Ltd
Category: homeopathic | Type: HUMAN OTC DRUG LABEL
Date: 20250718

ACTIVE INGREDIENTS: POTASSIUM CHLORIDE 6 [hp_X]/1 1
INACTIVE INGREDIENTS: MAGNESIUM STEARATE; LACTOSE MONOHYDRATE; ANHYDROUS DIBASIC CALCIUM PHOSPHATE

Active Ingredients Purpose

Kali Muriaticum 6X HPUS relief of symptoms associated with mucus congestion, coughs, mild sore throat

" HPUS" is the Homeopathic Pharmacopoeia of the United States

Uses

Temporarily relieves symptoms associated with

- Mucus congestion
- coughs
- Mild sore throat

Warnings

Sore throat warning:If sore throat is severe, persists more than 2 days, is accompanied or followed by a fever, headche, rash, nausea or vomiting, consult a doctor promptly.

Ask a doctor before use if you have

- Persistent or chronic cough, such as smoking, asthma, chronic bronchitis or emphysema
- A persistent cough may be a sign of a serious condition
- cough that is accompained by excessive phlegm (mucus)

Stop use and ask a doctor if

- Symptoms persist for more than 7 days or worsen
- Inflammation, fever or infection is present or develops
- Cough tends to recur or is accompanied by fever, rash or persistent headache.

If pregnant or breastfeeding, ask a health professional before use. Keep out of reach of children.

Directions

- Use as directed
- Take 30 minutes away from food

Adults: Acute dose: Chew 1 tablet every 30 minutes until symptoms subside up to 6 times per day.

Maintenance dose: Chew 1 tablet, 4 times daily.

Children 6 years and older: Acute dose: Crush 1/2 tablet, dissolve in water, and take every 30 minutes until symptoms subside, up to six times per day.

Maintenance dose :Crush 1/2 tablet, dissolve in water, 4 times per day.

Other Information

Store below 86°F

Inactive Ingredients

Calcium hydrogen phosphate, Lactose, Magnesium stearate

Questions?www.schuesslertissuesalts.co or + 1-888-464-6775